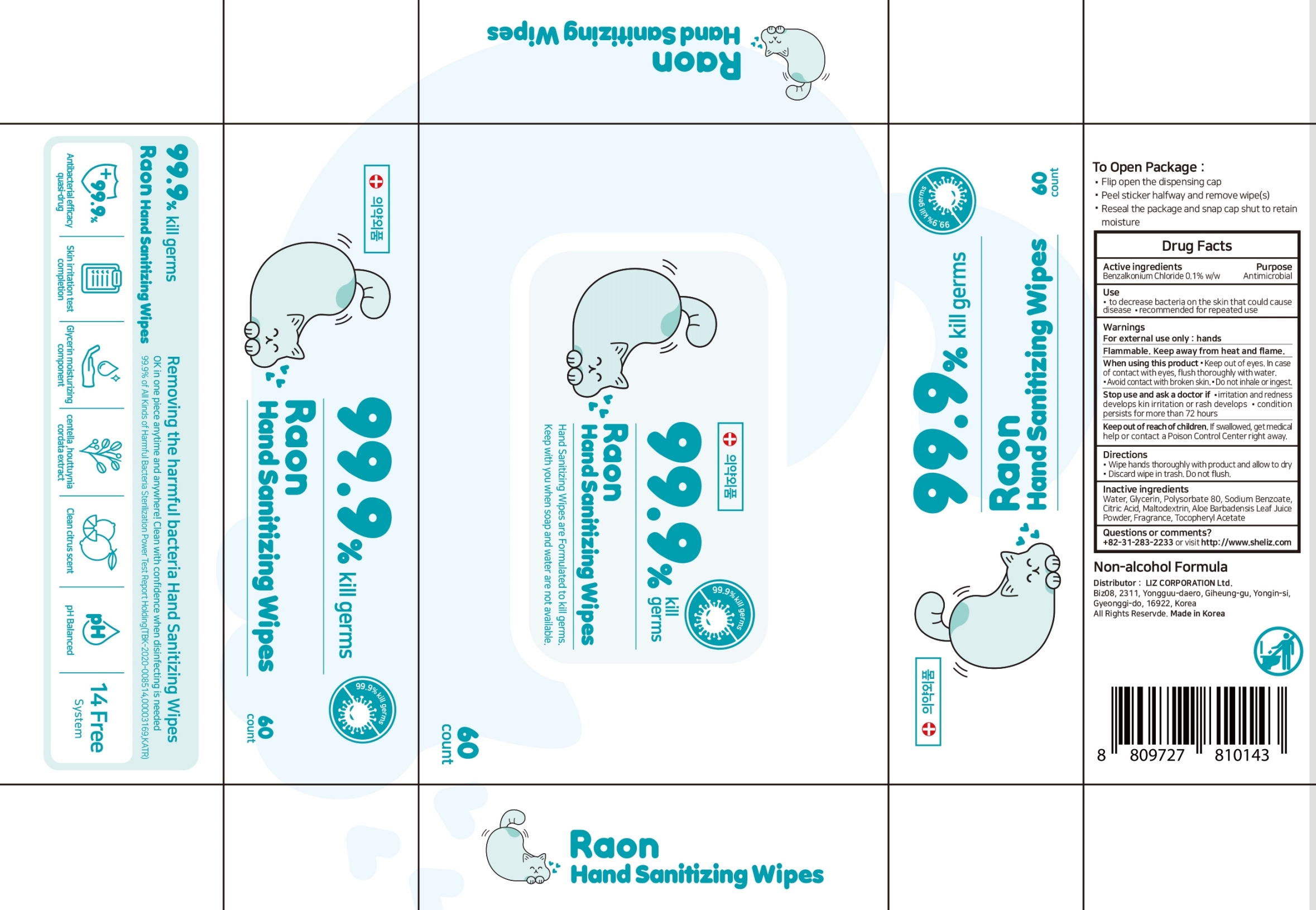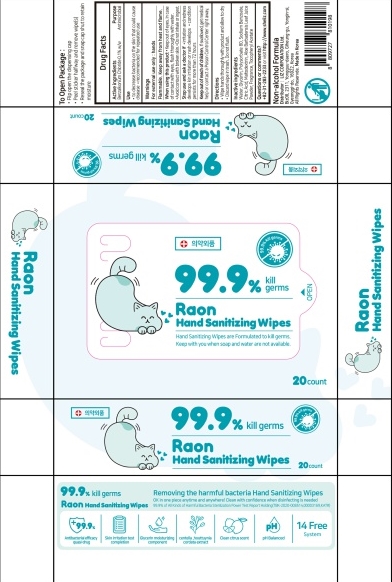 DRUG LABEL: Raon Hand Sanitizing Wipes
NDC: 79487-204 | Form: LIQUID
Manufacturer: Liz Corporation Co., Ltd
Category: otc | Type: HUMAN OTC DRUG LABEL
Date: 20210222

ACTIVE INGREDIENTS: BENZALKONIUM CHLORIDE 0.1 g/100 g
INACTIVE INGREDIENTS: WATER; CITRIC ACID MONOHYDRATE; MALTODEXTRIN; GLYCERIN; SODIUM BENZOATE; ALOE VERA LEAF; POLYSORBATE 80; .ALPHA.-TOCOPHEROL ACETATE

79487-204 Raon Hand Sanitizing Wipes

Active ingredients

Benzalkonium Chloride 0.1%

Purpose

Antimicrobial

Use

- to decrease bacteria on the skin that could cause disease
- recommended for repeated use

Warnings

For external use only : hands

Flammable. Keep away from heat and flame.

When using this product

- Keep out of eyes. In case of contact with eyse, flush thoroughly with water.
- Avoid contact with broken skin.
- Do not inhale or ingest.

Stop use and ask a doctor if

- irritation and redness develop skin irritation or rash develops
- condition persists for more than 72 hours

Keep out of reach of children.

If swallowed, get medical help or contact a Poison Control Center right away.

Directions

- Wipe hands thoroughly with product and allow to dry
- Discard wipe in trash. Do not flush.

Inactive ingredients

Water, Glycerin, Polysorbate 80, Sodium Benzoate, Citric Acid, Maltodextrin, Aloe Barbadensis Leaf Juice Powder, Fragrance, Tocopheryl Acetate